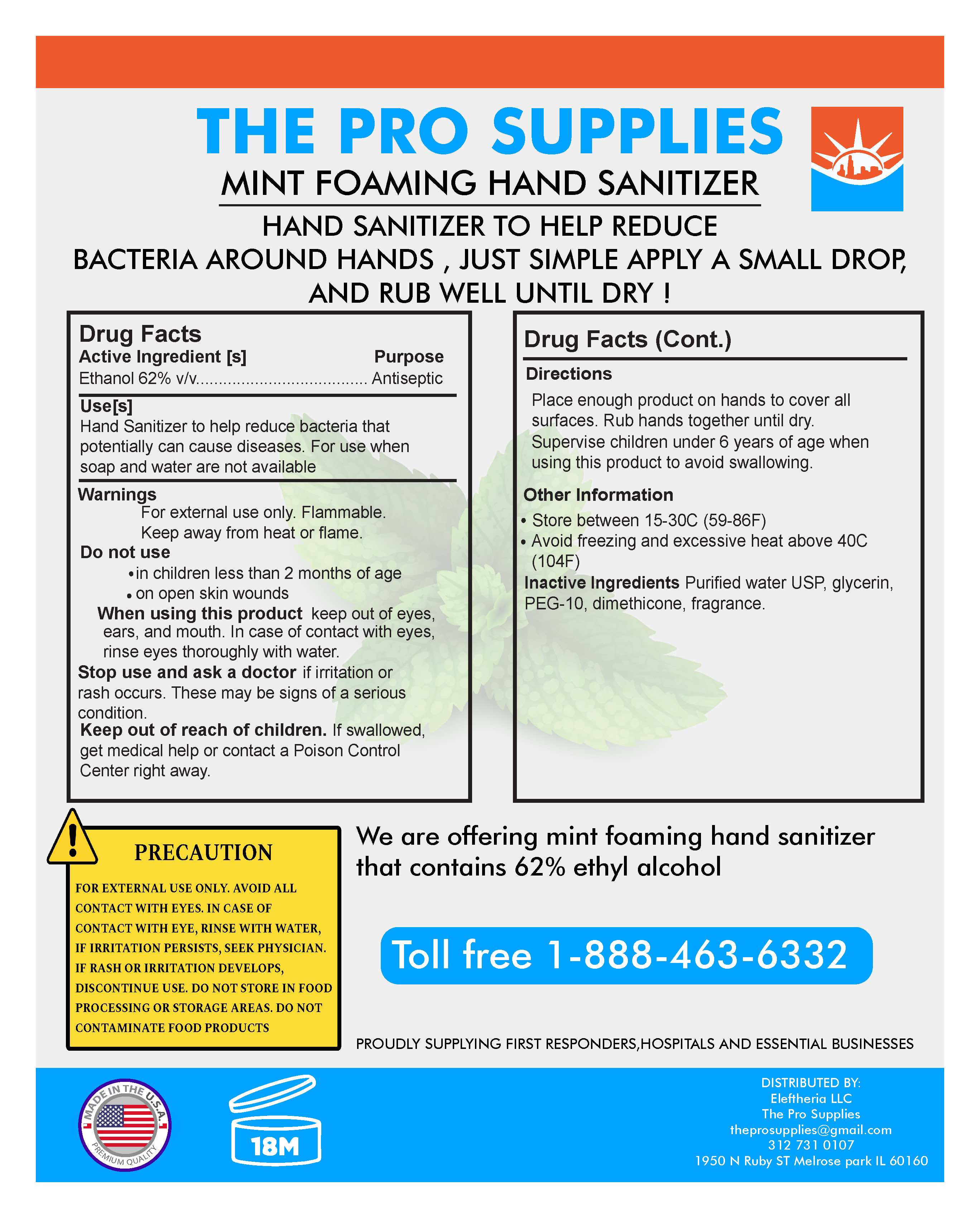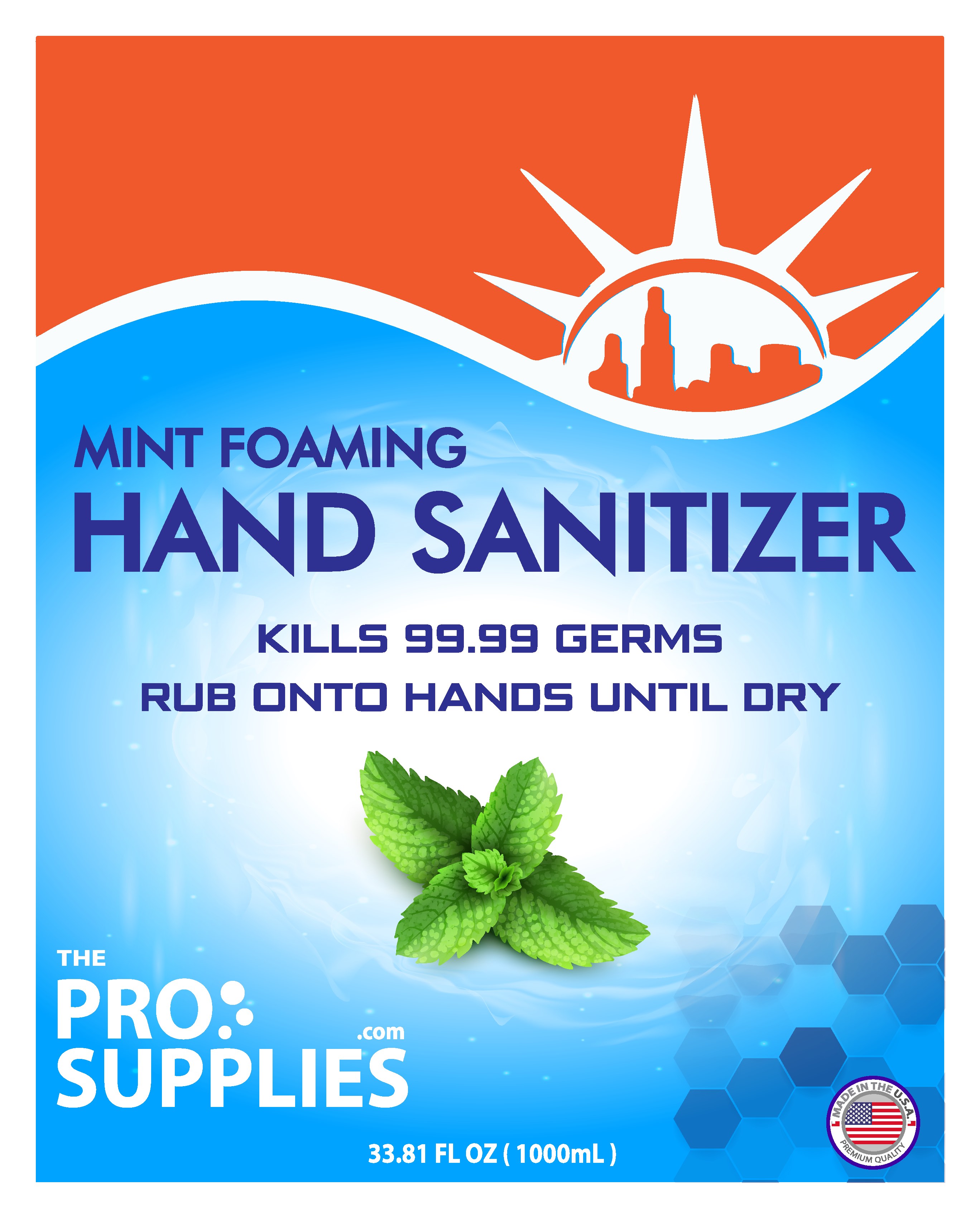 DRUG LABEL: Hand Sanitizer
NDC: 79667-001 | Form: SOLUTION
Manufacturer: ELEFTHERIA LLC
Category: otc | Type: HUMAN OTC DRUG LABEL
Date: 20211118

ACTIVE INGREDIENTS: ALCOHOL 62 mL/100 mL
INACTIVE INGREDIENTS: POLYETHYLENE GLYCOL 500; GLYCERIN; WATER; DIMETHICONE

Active Ingredient(s)

Ethanol 62% v/v.

Purpose

Antiseptic

Use

Hand Sanitizer to help reduce bacteria that potentially can cause disease. For use when soap and water are not available.

Warnings

For external use only. Flammable. Keep away from heat or flame

Do not use

- in children less than 2 months of age
- on open skin wounds

When using this product keep out of eyes, ears, and mouth. In case of contact with eyes, rinse eyes thoroughly with water.

Stop use and ask a doctor if irritation or rash occurs. These may be signs of a serious condition.

Keep out of reach of children. If swallowed, get medical help or contact a Poison Control Center right away.

Directions

- Place enough product on hands to cover all surfaces. Rub hands together until dry.
- Supervise children under 6 years of age when using this product to avoid swallowing.

Other information

- Store between 15-30C (59-86F)
- Avoid freezing and excessive heat above 40C (104F)

Inactive ingredients

Purified Water USP, Glycerin, PEG-10, Dimethicone, Fragrance

Package Label - Principal Display Panel

1000 mL NDC: 79667-001-10

1000 mL NDC: 79667-001-10